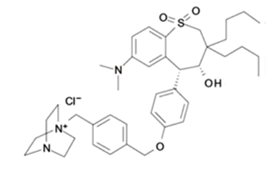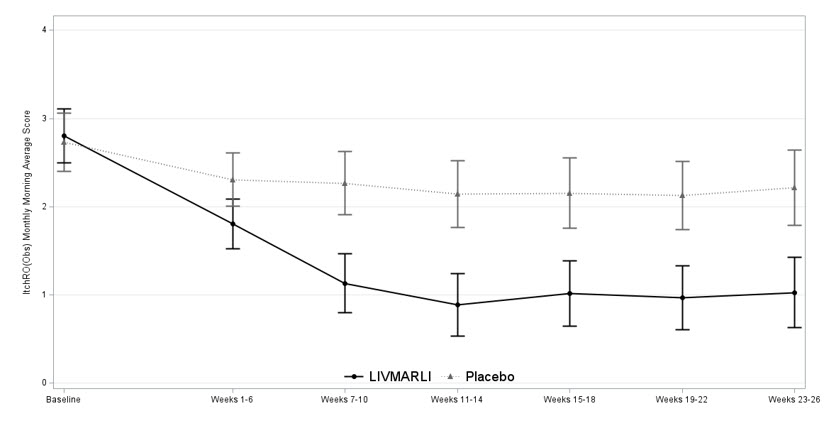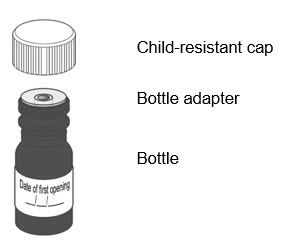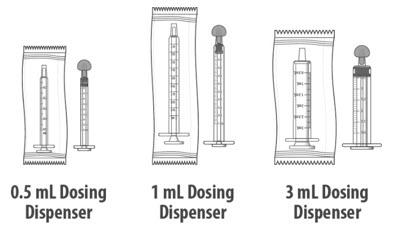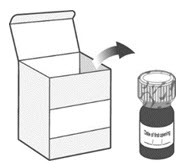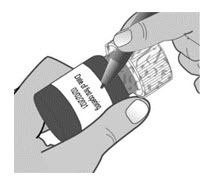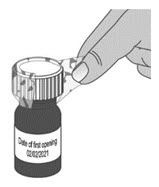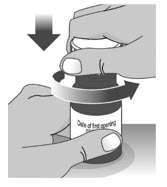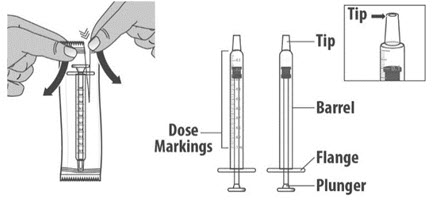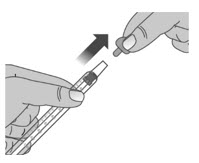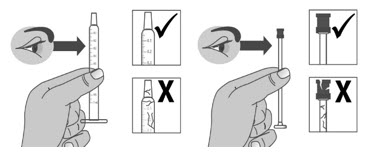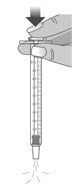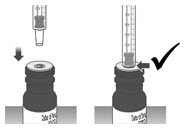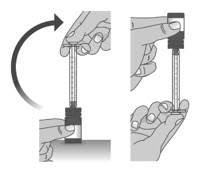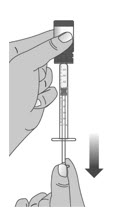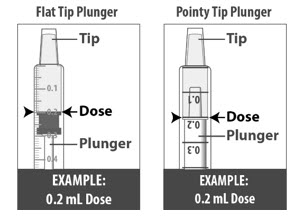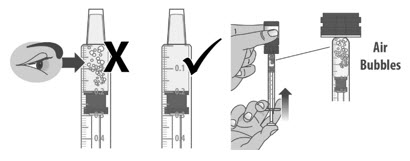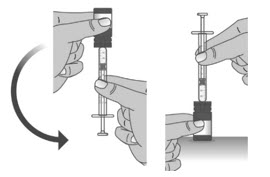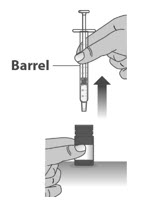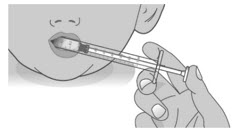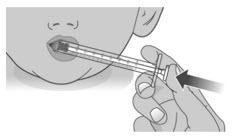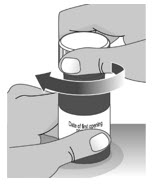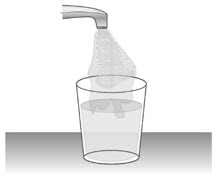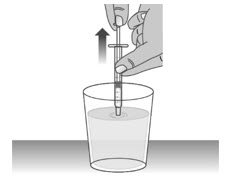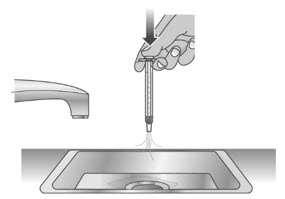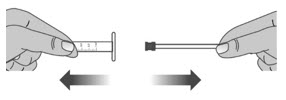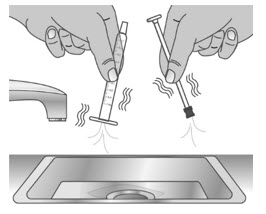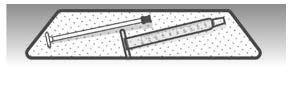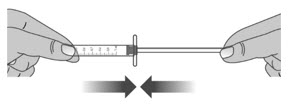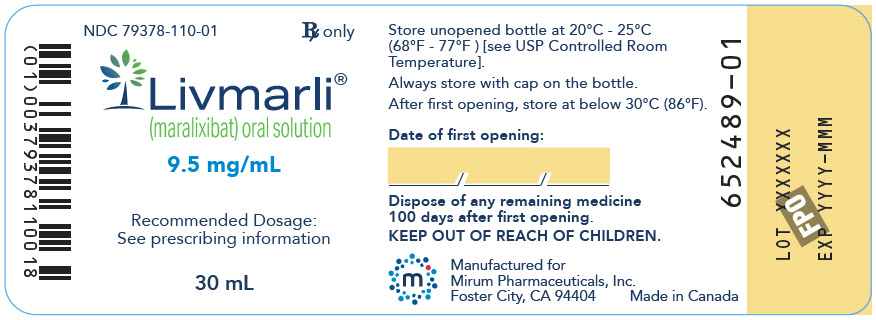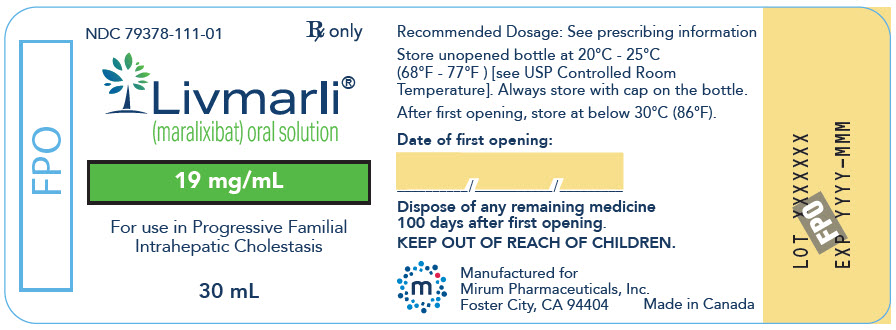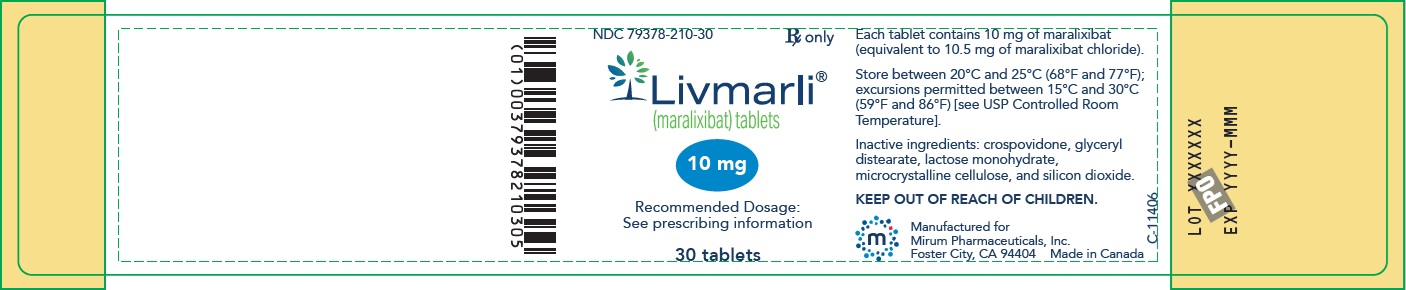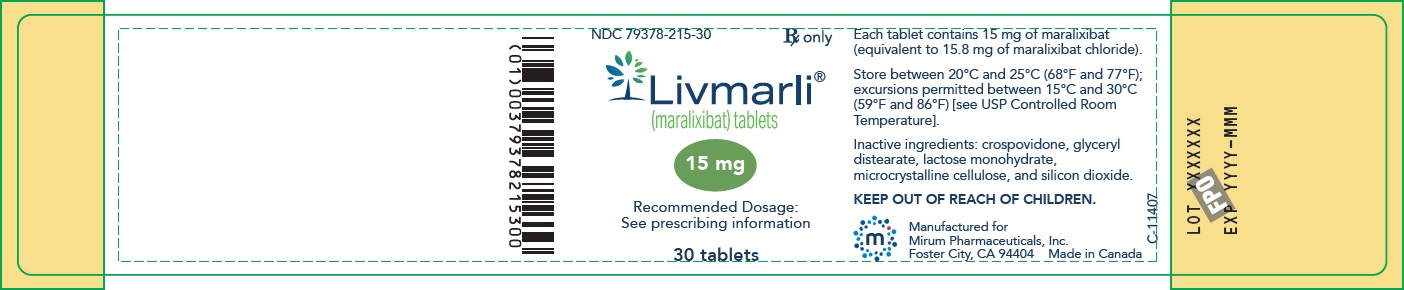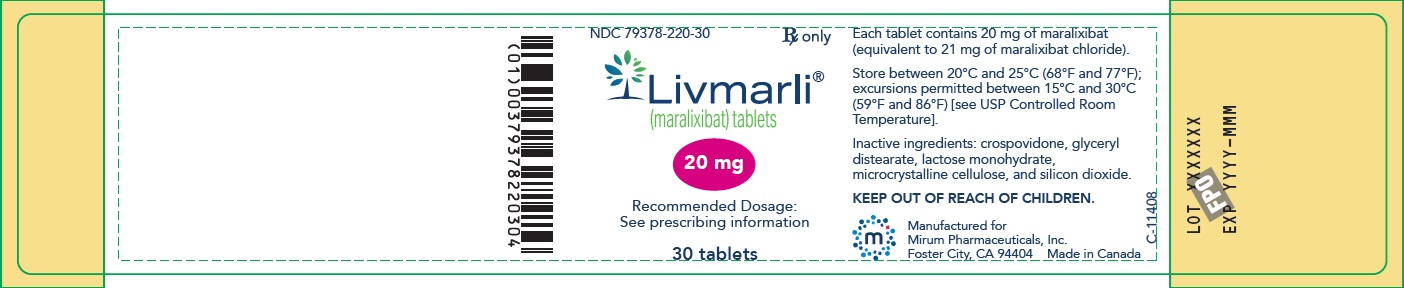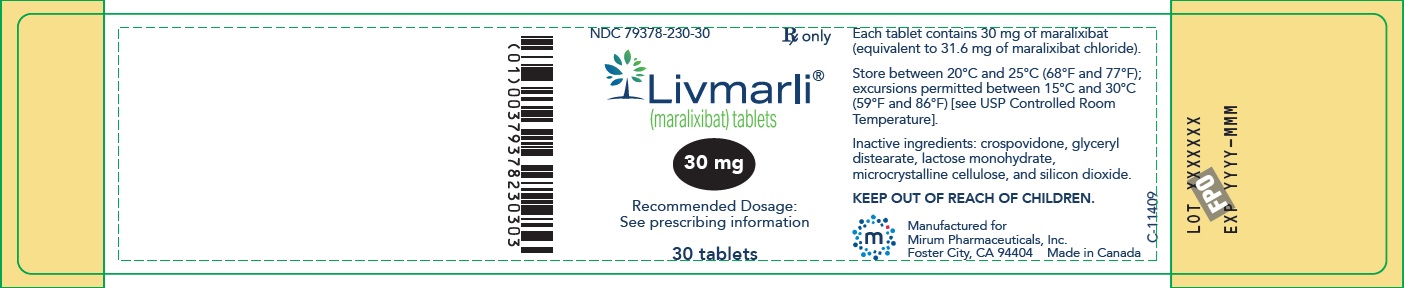 DRUG LABEL: Livmarli
NDC: 79378-110 | Form: SOLUTION
Manufacturer: Mirum Pharmaceuticals Inc.
Category: prescription | Type: HUMAN PRESCRIPTION DRUG LABEL
Date: 20250410

ACTIVE INGREDIENTS: maralixibat chloride 9.5 mg/1 mL
INACTIVE INGREDIENTS: Propylene Glycol; Sucralose; Edetate Disodium; Water

HIGHLIGHTS OF PRESCRIBING INFORMATION

These highlights do not include all the information needed to use LIVMARLI safely and effectively. See full prescribing information for LIVMARLI.
LIVMARLI® (maralixibat) oral solution
LIVMARLI® (maralixibat) tablets, for oral use
Initial U.S. Approval: 2021

RECENT MAJOR CHANGES

Dosage and Administration (2.1, 2.2, 2.3) | 4/2025
Warnings and Precautions (5.4) | 7/2024

1 INDICATIONS AND USAGE

LIVMARLI is an ileal bile acid transporter (IBAT) inhibitor indicated for:

- the treatment of cholestatic pruritus in patients 3 months of age and older with Alagille syndrome (ALGS). (1.1)
- the treatment of cholestatic pruritus in patients 12 months of age and older with progressive familial intrahepatic cholestasis (PFIC). (1.2)
  - Limitations of Use:
    LIVMARLI is not recommended in a subgroup of PFIC type 2 patients with specific ABCB11 variants resulting in non-functional or complete absence of bile salt export pump (BSEP) protein. (14.2)

2 DOSAGE AND ADMINISTRATION

- Use LIVMARLI Oral Solution 9.5 mg/mL for treatment of ALGS. (2.1)
- Use LIVMARLI Oral Solution 19 mg/mL for treatment of PFIC. (2.1)
- LIVMARLI Tablets can be used for treatment of both ALGS and PFIC in patients weighing 25 kg and above who can swallow tablets. (2.1)
ALGS:
  ○ The recommended dosage is 380 mcg/kg once daily, taken 30 minutes before a meal in the morning.
  ○ Starting dose is 190 mcg/kg orally once daily,and should be increased to 380 mcg/kg daily after one week, as tolerated and not to exceed a maximum daily dose of 28.5 mg per day for the oral solution and 30 mg per day for the tablets. (2.2)
PFIC:
  ○ The recommended dosage is 570 mcg/kg twice daily before a meal.
  ○ Starting dose is 285 mcg/kg orally once daily in the morning and should be increased to 285 mcg/kg twice daily, 428 mcg/kg twice daily, and then to 570 mcg/kg twice daily, as tolerated and not to exceed a maximum daily dose of 38 mg per day for the oral solution and 40 mg per day for the tablets. (2.3)
- See full prescribing information for additional dosage details for LIVMARLI oral solution and tablet formulations. (2.2, 2.3)

3 DOSAGE FORMS AND STRENGTHS

Oral solution:

- 9.5 mg of maralixibat per mL: treatment of ALGS. (3)
- 19 mg of maralixibat per mL: treatment of PFIC. (3)

Tablets: 10 mg, 15 mg, 20 mg, and 30 mg. (3)

4 CONTRAINDICATIONS

Patients with prior or active hepatic decompensation events (e.g., variceal hemorrhage, ascites, hepatic encephalopathy). (4)

5 WARNINGS AND PRECAUTIONS

- Hepatotoxicity: Obtain baseline liver tests and monitor patients frequently for the first 6 to 8 months after starting therapy, and as clinically indicated thereafter during treatment. If liver test abnormalities or signs of clinical hepatitis occur, consider dose reduction or treatment interruption. For persistent or recurrent liver test abnormalities relative to baseline, discontinue LIVMARLI. Monitor patients with compensated cirrhosis frequently. Permanently discontinue LIVMARLI if hepatic decompensation event occurs. (5.1)
- Gastrointestinal Adverse Reactions: Consider reducing the dosage or interrupting LIVMARLI treatment if a patient experiences persistent diarrhea or abdominal pain, or has diarrhea with bloody stool, vomiting, dehydration requiring treatment, or fever. Consider stopping LIVMARLI treatment if diarrhea or abdominal pain persists and no alternate etiology is identified. (5.2)
- Fat-Soluble Vitamin (FSV) Deficiency: Obtain baseline levels and monitor during treatment. Supplement if deficiency is observed. If FSV deficiency persists or worsens despite FSV supplementation, consider discontinuing LIVMARLI treatment. (5.3)
  - Fracture: Consider interrupting LIVMARLI treatment and supplement with FSV. LIVMARLI can be restarted once FSV deficiency is corrected and maintained at corrected levels.
  - Bleeding: Interrupt treatment with LIVMARLI. Treatment can be restarted if the FSV deficiency is corrected and bleeding has resolved.
- Risk of Propylene Glycol Toxicity (Pediatric Patients Less Than 5 years of Age): Total daily intake of propylene glycol should be considered for managing the risk of propylene glycol toxicity. Monitor patients for signs of propylene glycol toxicity. Discontinue if toxicity is suspected. (5.4)

6 ADVERSE REACTIONS

Most common adverse reactions (≥5%) are:

- ALGS: diarrhea, abdominal pain, vomiting, fat-soluble vitamin deficiency, liver test abnormalities, and bone fractures. (6.1)
- PFIC: diarrhea, fat soluble vitamin deficiency, abdominal pain, liver test abnormalities, hematochezia, and bone fractures. (6.1)

To report SUSPECTED ADVERSE REACTIONS, contact Mirum Pharmaceuticals at 1-855-MRM-4YOU or FDA at 1-800-FDA-1088 or www.fda.gov/medwatch.

7 DRUG INTERACTIONS

- Bile Acid Sequestrants: Modify LIVMARLI administration schedule. (7.1)

FULL PRESCRIBING INFORMATION

1 INDICATIONS AND USAGE

1.1 Treatment of Cholestatic Pruritus in Patients with Alagille Syndrome

LIVMARLI® is indicated for the treatment of cholestatic pruritus in patients 3 months of age and older with Alagille syndrome (ALGS).

1.2 Treatment of Cholestatic Pruritus in Patients with Progressive Familial Intrahepatic Cholestasis

LIVMARLI is indicated for the treatment of cholestatic pruritus in patients 12 months of age and older with progressive familial intrahepatic cholestasis (PFIC).

Limitations of Use:
  LIVMARLI is not recommended in a subgroup of PFIC type 2 patients with specific ABCB11 variants resulting in non-functional or complete absence of bile salt export pump (BSEP) protein [see Clinical Studies (14.2)].

2 DOSAGE AND ADMINISTRATION

2.1 Important Administration Information

- Use LIVMARLI Oral Solution 9.5 mg/mL for treatment of ALGS.
- Use LIVMARLI Oral Solution 19 mg/mL for treatment of PFIC.
- The two strengths of LIVMARLI Oral Solution, 9.5 mg/mL and 19 mg/mL, should not be substituted for one another when treating PFIC patients [see Dosage and Administration (2.3)].
- LIVMARLI tablets can be used for treatment of both ALGS and PFIC in patients weighing 25 kg and above who can swallow tablets. Select LIVMARLI Oral Solution or LIVMARLI Tablets based on the patient's weight and ability to swallow tablets [see Dosage and Administration (2.2, 2.3)].

2.2 Recommended Dosage for Alagille Syndrome

Use LIVMARLI Oral Solution 9.5 mg/ mL or LIVMARLI Tablets for the treatment of ALGS.

The recommended dosage is 380 mcg/kg once daily, taken 30 minutes before a meal in the morning. Start dosing at 190 mcg/kg administered orally once daily; after one week, increase to 380 mcg/kg once daily, as tolerated. The maximum daily dose should not exceed 28.5 mg (3 mL) per day for LIVMARLI Oral solution and 30 mg per day for LIVMARLI tablets. Refer to the dosage by weight guidelines presented in Table 1 for LIVMARLI Oral Solution and Table 2 for LIVMARLI tablets.

Table 1: 9.5 mg/mL LIVMARLI Oral Solution for Patients with ALGS: Volume per Dose (mL) by Weight
Patient Weight (kg) | Days 1-7 (190 mcg/kg once daily) | Beginning Day 8 (380 mcg/kg once daily)
Patient Weight (kg) | 9.5 mg/mL Solution (for ALGS); Volume per Dose (mL)
5 to 6 | 0.1 | 0.2
7 to 9 | 0.15 | 0.3
10 to 12 | 0.2 | 0.45
13 to 15 | 0.3 | 0.6
16 to 19 | 0.35 | 0.7
20 to 24 | 0.45 | 0.9
25 to 29 | 0.5 | 1
30 to 34 | 0.6 | 1.25
35 to 39 | 0.7 | 1.5
40 to 49 | 0.9 | 1.75
50 to 59 | 1 | 2.25
60 to 69 | 1.25 | 2.5
70 or higher | 1.5 | 3

Table 2: LIVMARLI Tablets for Patients with ALGS: Dosage by Weight*
Patient Weight (kg) | Days 1 to 7 (190 mcg/kg QD) | Beginning Day 8 (380 mcg/kg QD)
Less than 25 | Use Oral Solution | Use Oral Solution
25 to 32 | Use Oral Solution | 10 mg
33 to 43 | Use Oral Solution | 15 mg
44 to 65 | 10 mg | 20 mg
66 or higher | 15 mg | 30 mg
*Select the appropriate product based on the patient's weight and ability to swallow tablets.

2.3 Recommended Dosage for Progressive Familial Intrahepatic Cholestasis

Use LIVMARLI Oral Solution 19 mg/mL or LIVMARLI Tablets for the treatment of PFIC.

The two strengths of LIVMARLI, 9.5 mg/mL and 19 mg/mL, should not be substituted for one another when treating PFIC patients. Special attention should be given to the accurate calculation of the dose volume of LIVMARLI. This is especially important for pediatric patients less than 5 years old as LIVMARLI oral solution contains the excipient propylene glycol (364.5 mg/mL) [see Warnings and Precautions (5.4) and Overdosage (10)].

The recommended dosage is 570 mcg/kg twice daily 30 minutes before a meal. The starting dose is 285 mcg/kg orally once daily in the morning, and should be increased to 285 mcg/kg twice daily, 428 mcg/kg twice daily, and then to 570 mcg/kg twice daily, as tolerated. The maximum daily dose should not exceed 38 mg (2 mL) per day for LIVMARLI oral solution and 40 mg per day for LIVMARLI tablets. Refer to the dosing by weight guidelines presented in Table 3 for LIVMARLI oral solution and Table 4 for LIVMARLI tablets.

Table 3: 19 mg/mL LIVMARLI Oral Solution for Patients with PFIC: Volume per Dose (mL) by Weight
Patient Weight; (kg) | 285 mcg/kg; (once daily titrated to twice daily) | 428 mcg/kg; (twice daily) | 570 mcg/kg; (twice daily as tolerated)
Patient Weight; (kg) | 19 mg/mL Solution (for PFIC); Volume per Dose (mL)
5 | 0.1 | 0.1 | 0.15
6 to 7 | 0.1 | 0.15 | 0.2
8 | 0.1 | 0.2 | 0.25
9 | 0.15 | 0.2 | 0.25
10 to 12 | 0.15 | 0.25 | 0.3
13 to 15 | 0.2 | 0.3 | 0.4
16 to 19 | 0.25 | 0.4 | 0.5
20 to 24 | 0.3 | 0.5 | 0.6
25 to 29 | 0.4 | 0.6 | 0.8
30 to 34 | 0.45 | 0.7 | 0.9
35 to 39 | 0.6 | 0.8 | 1
40 to 49 | 0.6 | 0.9 | 1
50 to 59 | 0.8 | 1 | 1
60 or higher | 0.9 | 1 | 1

Table 4: LIVMARLI Tablets for Patients with PFIC: Dosage by Weight*
Patient Weight (kg) | 285 mcg/kg BID | 428 mcg/kg BID | 570 mcg/kg BID
Less than 25 | Use Oral Solution | Use Oral Solution | Use Oral Solution
25 to 32 | Use Oral Solution | Use Oral Solution | 15 mg
33 to 43 | 10 mg | 15 mg | 20 mg
44 or higher | 15 mg | 20 mg | 20 mg
*Select the appropriate product based on the patient's weight and ability to swallow tablets.

2.4 Missed Dose

For once daily dosing: If a dose is missed, it should be taken as soon as possible within 12 hours of the time it is usually taken, and the original dosing schedule should be resumed. If a dose is missed by more than 12 hours, the dose can be omitted and the original dosing schedule resumed.

For twice daily dosing: If a dose is missed, it should be taken as soon as possible within 6 hours of the time it is usually taken, and the original dosing schedule should be resumed. If a dose is missed by more than 6 hours, the dose can be omitted and the original dosing schedule resumed.

2.5 Important Administration Instructions

Administer LIVMARLI oral solution and tablets 30 minutes before a meal [see Clinical Pharmacology (12.3)].

A calibrated measuring device (0.5 mL, 1 mL or 3 mL oral dosing dispenser) for LIVMARLI oral solution will be provided by the pharmacy to measure and deliver the prescribed dose accurately.

After opening the LIVMARLI oral solution bottle, store below 30°C (86°F) and discard any remaining LIVMARLI oral solution after 100 days.

2.6 Dosage Modification for Management of Adverse Events

Establish the baseline pattern of variability of liver tests prior to starting LIVMARLI, so that potential signs of liver injury can be identified. Monitor liver tests (e.g., ALT [alanine aminotransferase], AST [aspartate aminotransferase], TB [total bilirubin]), DB [direct bilirubin], and International Normalized Ratio [INR]) during treatment with LIVMARLI. Reduce the dosage or interrupt LIVMARLI if new onset liver test abnormalities occur. Once the liver test abnormalities either return back to baseline values or stabilize at a new baseline value, consider restarting LIVMARLI at the last tolerated dose, and increase the dose as tolerated. Consider discontinuing LIVMARLI permanently if liver test abnormalities recur or symptoms consistent with clinical hepatitis are observed [see Warnings and Precautions (5.1)].

LIVMARLI has not been studied in patients with hepatic decompensation. Discontinue LIVMARLI permanently if a patient experiences a hepatic decompensation event (e.g., variceal hemorrhage, ascites, hepatic encephalopathy).

2.7 Administration Modification for Drug Interaction

Bile Acid Binding Resins

Administer LIVMARLI at least 4 hours before or 4 hours after administering the bile acid binding resins [see Drug Interactions (7.1)] when used concomitantly.

3 DOSAGE FORMS AND STRENGTHS

LIVMARLI Oral solution:

- 9.5 mg of maralixibat per mL (for treatment of ALGS) as a clear, colorless to yellow solution.
- 19 mg of maralixibat per mL (for treatment of PFIC) as a clear, colorless to yellow solution.

LIVMARLI Tablets:

- 10 mg: white to off-white round tablets debossed with MRX on one side, 10 on the other side.
- 15 mg: white to off-white modified oval tablets debossed with MRX on one side, 15 on the other side.
- 20 mg: white to off-white round tablets debossed with MRX on one side, 20 on the other side.
- 30 mg: white to off-white round tablets debossed with MRX on one side, 30 on the other side.

4 CONTRAINDICATIONS

LIVMARLI is contraindicated in patients with prior or active hepatic decompensation events (e.g., variceal hemorrhage, ascites, hepatic encephalopathy) [see Warnings and Precautions (5.1)].

5 WARNINGS AND PRECAUTIONS

5.1 Hepatotoxicity

LIVMARLI treatment is associated with a potential for drug-induced liver injury.

In the PFIC trial, treatment-emergent hepatic decompensation events and elevations of liver tests or worsening of liver tests occurred. Two patients experienced drug-induced liver injury (DILI) attributable to LIVMARLI. Two additional patients experienced DILI in the open-label extension portion of the trial. Of these four patients, one patient required liver transplant and another patient died.

In the ALGS trial, treatment-emergent elevations of liver tests or worsening of liver tests occurred. Most abnormalities included elevations in ALT, AST, and/or TB/DB. One patient whose TB was elevated at baseline discontinued LIVMARLI after 28 weeks due to increased TB above baseline. Four patients had ALT increases that led to dose modification (n=1), dose interruption (n=2), or permanent discontinuation (n=2) of LIVMARLI during the long-term, open-label extension period [see Adverse Reactions (6.1)].

Obtain baseline liver tests because some ALGS and PFIC patients have abnormal liver tests at baseline. Monitor patients frequently for the first 6 to 8 months after starting therapy and as clinically indicated thereafter during treatment with LIVMARLI. Monitor for elevations in liver tests, for the development of liver-related adverse reactions, and for physical signs of hepatic decompensation. If liver test abnormalities or signs of clinical hepatitis occur in the absence of other causes, consider dose reduction or treatment interruption.

Permanently discontinue LIVMARLI if a patient experiences the following:

- persistent or recurrent liver test abnormalities, or
- upon rechallenge, signs and symptoms consistent with clinical hepatitis, or
- a hepatic decompensation event.

The safety and effectiveness of LIVMARLI have not been established in patients with decompensated cirrhosis. Monitor patients with compensated cirrhosis frequently and discontinue LIVMARLI if hepatic decompensation occurs. LIVMARLI is contraindicated in patients with prior or active hepatic decompensation events [see Contraindications (4)].

5.2 Gastrointestinal Adverse Reactions

Diarrhea and abdominal pain were reported as the most common adverse reactions in patients treated with LIVMARLI [see Adverse Reactions (6.1)].

Consider reducing the dosage or interrupting LIVMARLI treatment if a patient experiences persistent diarrhea or abdominal pain, or has diarrhea with bloody stool, vomiting, dehydration requiring treatment, or fever. Consider stopping LIVMARLI treatment if diarrhea or abdominal pain persists and no alternate etiology is identified. Monitor for dehydration due to diarrhea and treat promptly. LIVMARLI was not evaluated in PFIC patients with chronic diarrhea requiring intravenous fluids.

When diarrhea or abdominal pain resolves, restart LIVMARLI at the last tolerated dose and increase the dose as tolerated. Consider stopping LIVMARLI treatment if they recur upon re-challenge with LIVMARLI.

5.3 Fat Soluble Vitamin (FSV) Deficiency

LIVMARLI may adversely affect absorption of fat-soluble vitamins (FSV). FSV include vitamins A, D, E, and K (measured using INR levels). ALGS and PFIC patients can have FSV deficiency at baseline and are frequently supplemented with FSV.

In ALGS patients in Trial 1, treatment-emergent FSV deficiency was reported in 3 (10%) patients during 48 weeks of treatment.

In PFIC patients in Trial 2, treatment-emergent FSV deficiency (assessed biochemically) was reported in 13 (28%) of LIVMARLI-treated patients versus 16 (35%) of placebo-treated patients during 26 weeks of treatment.

Bone Fracture

Treatment-emergent bone fracture events have been observed more frequently with LIVMARLI-treated patients compared to placebo-treated patients [see Adverse Reactions (6.1)]. If fracture occurs, consider interrupting LIVMARLI treatment and supplement with FSV. LIVMARLI can be restarted once FSV deficiency is corrected and maintained at corrected levels.

Bleeding

If bleeding occurs, interrupt treatment with LIVMARLI. LIVMARLI can be restarted if FSV deficiency is corrected and bleeding has resolved.

Obtain serum FSV levels prior to initiation of LIVMARLI and monitor the levels periodically during treatment, along with any clinical manifestations of FSV deficiency. Supplement with FSV if FSV deficiency is diagnosed. Consider discontinuing LIVMARLI if FSV deficiency persists or worsens despite adequate FSV supplementation.

If complications of FSV deficiency occur, such as fracture or bleeding, consider interrupting LIVMARLI treatment and supplement with FSV. LIVMARLI can be restarted once FSV deficiency is corrected and maintained at corrected levels.

5.4 Risk of Propylene Glycol Toxicity (Pediatric Patients Less Than 5 Years of Age)

LIVMARLI oral solution contains propylene glycol. Patients less than 5 years of age are at highest risk for propylene glycol toxicity, and a safe level for propylene glycol exposure with repeated administration has not been established for pediatric patients less than 5 years of age. When LIVMARLI oral solution is administered at the dose (380 mcg/kg once daily) for treatment of cholestatic pruritus in patients with ALGS, the exposure to propylene glycol will be 14.6 mg/kg/day. When LIVMARLI oral solution is administered at the dose (570 mcg/kg twice daily) for treatment of cholestatic pruritus in patients with PFIC, the exposure to propylene glycol will be 21.9 mg/kg/day. The total daily intake of propylene glycol from all sources should be considered for managing the risk of propylene glycol toxicity.

Monitor patients for signs of potential propylene glycol toxicity, including hemolysis, hyperosmolarity with anion gap metabolic acidosis, acute kidney injury, and CNS toxicity. Discontinue LIVMARLI oral solution if propylene glycol toxicity is suspected [see Overdosage (10)].

6 ADVERSE REACTIONS

The following clinically significant adverse reactions are described elsewhere in labeling:

- Hepatotoxicity [see Warnings and Precautions (5.1)]
- Gastrointestinal Adverse Reactions [see Warnings and Precautions (5.2)]
- Fat Soluble Vitamin (FSV) Deficiency [see Warnings and Precautions (5.3)]

6.1 Clinical Trials Experience

Because clinical trials are conducted under widely varying conditions, adverse reaction rates observed in the clinical trials of a drug cannot be directly compared to rates in the clinical trials of another drug and may not reflect the rates observed in practice.

ALGS:

In the Alagille syndrome clinical development program, which includes five clinical studies comprising 86 patients, patients received doses of LIVMARLI up to 760 mcg/kg per day with a median duration of exposure of 32.3 months (range: 0.03 – 60.9 months). In Trial 1, the 4-week placebo control period occurred after 18 weeks of LIVMARLI treatment. In two supportive studies that included long-term open‑label extensions, only 13 weeks of placebo-controlled treatment occurred which evaluated doses lower than 380 mcg/kg/day. The majority of LIVMARLI exposure in the development program occurred without a placebo control in open-label trial extensions.

The most common adverse reactions (≥5%) for ALGS patients treated with LIVMARLI are presented in Table 5 below. Treatment interruptions or dose reductions occurred in 5 (6%) patients due to diarrhea, abdominal pain, or vomiting.

Table 5: Adverse Reactions Occurring in ≥ 5% of Patients Treated with LIVMARLI in the ALGS Clinical Development Program
LIVMARLI (n=86)
Adverse Reaction | Any Grade; n (%) | Number of events per 100 person‑years^1
Diarrhea | 48 (55.8%) | 41.6
Abdominal pain* | 46 (53.5%) | 38.6
Vomiting | 35 (40.7%) | 19.8
Nausea | 7 (8.1%) | 2.9
Fat-Soluble Vitamin deficiency* | 22 (25.6%) | 11.1
Transaminases increased (ALT, AST)* | 16 (18.6%) | 6.9
Bone Fractures* | 8 (9.3%) | 3.3
*Terms were defined as:
Fat-Soluble Vitamin deficiency includes: A, D, E, or K deficiency, or INR increase
Abdominal Pain includes: abdominal discomfort, abdominal distension, abdominal pain, abdominal pain lower, abdominal pain upper
Transaminases increased includes: ALT abnormal, ALT increased, AST abnormal, AST increased
Bone Fracture includes: tibia fracture, rib fracture, hand fracture, humerus fracture, pathological fracture, forearm fracture, clavicle fracture
^1 Exposure adjusted incidence rate for each adverse reaction type was calculated using the first occurrence of this adverse reaction per patient

Liver Test Abnormalities

Increase in Transaminases

In a pooled analysis of patients with ALGS (N=86) administered LIVMARLI, increases in hepatic transaminases (ALT) were observed. Seven (8.1%) patients discontinued LIVMARLI due to ALT increases. Three (3.5%) patients had a decrease in dose or interruption of LIVMARLI in response to ALT increases. In the majority of cases, the elevations resolved or improved after discontinuation or dose modification of LIVMARLI. In some cases, the elevations resolved or improved without change in LIVMARLI dosing. Increases to more than three times baseline in ALT occurred in 26% of patients treated with LIVMARLI and increases to more than five times baseline occurred in 3%. AST increases to more than three times baseline occurred in 16% of patients treated with LIVMARLI, and an increase to more than five times baseline occurred in one patient. Elevations in transaminases were asymptomatic and not associated with bilirubin elevations or other laboratory abnormalities.

Increases in Bilirubin

Four (4.6%) patients in the pooled analysis experienced bilirubin increases above baseline, and LIVMARLI was subsequently withdrawn in two of these patients, who had elevated bilirubin at baseline.

PFIC:

In Trial 2, which enrolled 93 patients, 47 patients received doses of LIVMARLI up to 570 mcg/kg BID, with a median duration of exposure of 6 months (range: 0.3-6.7 months).

The most common adverse reactions (≥5%) for PFIC patients treated with LIVMARLI at a rate greater than placebo are presented in Table 6 below. Diarrhea was the most frequent adverse reaction; the majority of episodes were mild and transient with a median duration of 5.5 days. Nineteen (40.4%) LIVMARLI-treated subjects had diarrhea greater than or equal to 7 days. Placebo-treated subjects had a median duration of 3 days of diarrhea and two subjects (4.3%) experienced diarrhea with a duration greater than or equal to 7 days. There were no severe events reported. The majority of abdominal pain events were mild based on AE grading, and associated with concurrent diarrhea.

One LIVMARLI-treated patient with an event of mild diarrhea discontinued treatment. Treatment interruptions or dose reductions occurred in 3 (6.4%) LIVMARLI-treated patients due to diarrhea or abdominal pain. No placebo-treated subjects discontinued treatment or had dose reductions or interruptions due to diarrhea.

Table 6: Adverse Reactions (any grade) Occurring in ≥5% and at a Rate Greater Than Placebo in Patients Treated with LIVMARLI in the PFIC Trial
Adverse Reaction; (Any Grade) | Placebo; n=46 | LIVMARLI; n=47
Diarrhea | 9 (19.6%) | 27 (57.4%)
Abdominal pain† | 7 (15.2%) | 13 (27.7%)
Transaminases increased (ALT or AST) † | 3 (6.5%) | 8 (17%)
Hematochezia or rectal hemorrhage | 1 (2.2%) | 4 (8.5%)
Bone Fractures† | 0 | 3 (6.4%)
† Terms were defined as:
Abdominal Pain includes: abdominal pain, abdominal pain upper, abdominal distension
Transaminases increased includes: Hypertransaminasaemia, ALT abnormal, ALT increased, AST abnormal, AST increased, Transaminases increased, Hepatic enzyme increased.
Bone Fracture includes: upper limb fracture, lower limb fracture, radius fracture, ulna fracture, femur fracture, foot fracture

Hepatotoxicity

LIVMARLI treatment is associated with a potential for drug-induced liver injury. In PFIC patients in Trial 2, treatment-emergent elevations of liver tests or worsening of liver tests, relative to baseline values, and hepatic decompensation events were observed. Two patients experienced drug-induced liver injury (DILI) attributable to LIVMARLI; one patient received 570 mcg/kg twice daily and the second patient required dose interruption and reduction. Two additional patients experienced DILI in the open-label extension portion of the trial. Of these four patients, one patient required liver transplant and another patient died.

Biliary Complications

In the placebo-controlled portion of Trial 2, two LIVMARLI-treated patients developed cholangitis or cholecystitis within 3-weeks of drug discontinuation (after 84 days and 130 days after initiating LIVMARLI treatment, respectively). Four LIVMARLI-treated patients developed cholecystitis or cholangitis in the open-label extension portion of Trial 2; the average time to onset was 281 days.

Bone Fracture

In PFIC patients in Trial 2, treatment-emergent bone fracture events were observed. Three receiving LIVMARLI experienced bone fractures relative to none in placebo-treated patients. The median time to onset of fractures was 73 days. Two LIVMARLI-treated patients developed bone fractures in the open-label portion of Trial 2, with average time to onset of fracture was 204 days.

Bleeding

In PFIC patients in Trial 2, treatment-emergent events of hematochezia (4 [8.5%] versus 1 [2.2%]), decrease in hemoglobin greater than or equal to 2 grams/dL from baseline (8 [17%] versus 1 [2.2%]), were reported more frequently in LIVMARLI-treated patients relative to placebo-treated patients

6.2 Postmarketing Experience

The following adverse reactions have been identified during post approval use of LIVMARLI. Because these reactions are reported voluntarily from a population of uncertain size, it is not always possible to reliably estimate their frequency or establish a causal relationship to drug exposure.

Gastrointestinal disorders: hematemesis, liver transplant, post-endoscopy hemorrhage, post-liver biopsy hemorrhage

General disorders and administration site conditions: drug ineffective

Injury, poisoning and procedural complications: off label use

Investigations: gamma-glutamyltransferase increased

Nervous system disorders: intracranial hemorrhage

7 DRUG INTERACTIONS

7.1 Effects of Other Drugs on LIVMARLI

Bile Acid Binding Resins

Bile acid binding resins may bind to maralixibat in the gut. Administer LIVMARLI at least 4 hours before or 4 hours after administration of bile acid binding resins (e.g., cholestyramine, colesevelam, or colestipol).

7.2 Effects of LIVMARLI on Other Drugs

OATP2B1 substrates

Maralixibat is an OATP2B1 inhibitor based on in vitro studies. A decrease in the oral absorption of OATP2B1 substrates (e.g., statins) due to OATP2B1 inhibition in the GI tract cannot be ruled out. Consider monitoring the drug effects of OATP2B1 substrates (e.g. statins) as needed [see Clinical Pharmacology (12.3)].

8 USE IN SPECIFIC POPULATIONS

8.1 Pregnancy

Risk Summary

Maternal use at the recommended clinical dose of LIVMARLI is not expected to result in measurable fetal exposure because systemic absorption following oral administration is low [see Clinical Pharmacology (12.3)]. Maralixibat may inhibit the absorption of fat-soluble vitamins [see Warnings and Precautions (5.3) and Clinical Considerations]. In animal reproduction studies, no developmental effects were observed (see Data).

The estimated background risk of major birth defects for ALGS is higher than the general population because ALGS is an autosomal dominant condition. The background risk of miscarriage for ALGS is unknown. The background risk of birth defects and miscarriage for PFIC is unknown. In the U.S. general population, the estimated background risk of major birth defects and miscarriage in clinically recognized pregnancies is 2% to 4% and 15% to 20%, respectively.

Clinical Considerations

Fetal/Neonatal Adverse Reactions

Maralixibat may inhibit the absorption of fat-soluble vitamins (FSV). Monitor for FSV deficiency and supplement as needed. Increased supplementation of FSVs may be needed during pregnancy [see Warnings and Precautions (5.3)].

Data

Animal Data

No effects on embryo-fetal development were observed in pregnant rats treated orally with up to 1000 mg/kg/day (approximately 3300 to 12000 times the maximum recommended dose based on AUC [area under the plasma concentration-time curve]) or in pregnant rabbits treated orally with up to 250 mg/kg/day (approximately 1200 to 4700 times the maximum recommended dose based on AUC) during the period of organogenesis. No effects on postnatal development were observed in a pre- and postnatal development study, in which female rats were treated orally with up to 750 mg/kg/day during organogenesis through lactation. Maternal systemic exposure to maralixibat at the maximum dose tested was approximately 2500 to 9400 times the maximum recommended dose based on AUC.

8.2 Lactation

Risk Summary

LIVMARLI has low absorption following oral administration, and breastfeeding is not expected to result in exposure of the infant to LIVMARLI at the recommended dose [see Clinical Pharmacology (12.3)]. There are no data on the presence of LIVMARLI in human milk, the effects on the breastfed infant, or the effects on milk production. Patients with ALGS or PFIC can have FSV deficiency as part of their disease. Maralixibat may reduce absorption of fat-soluble vitamins [see Warnings and Precautions (5.3)]. Monitor FSV levels and supplement FSV intake, if FSV deficiency is observed during lactation. The developmental and health benefits of breastfeeding should be considered along with the mother’s need for LIVMARLI and any potential adverse effects on the breastfed child from LIVMARLI or from the underlying maternal condition.

8.4 Pediatric Use

ALGS

The safety and effectiveness of LIVMARLI for the treatment of cholestatic pruritus in Alagille syndrome have been established in pediatric patients aged 3 months of age and older. Use of LIVMARLI in this population is supported by evidence from a study of patients 1 to 15 years of age (N=31) that included 18 weeks of open-label treatment followed by a 4 week placebo-controlled randomized withdrawal period and a subsequent 26-week open-label treatment period. Additional safety information was obtained from four studies in patients up to 21 years of age (N=55) [see Adverse Reactions (6.1) and Clinical Studies (14.1)]. Use of LIVMARLI in patients 3 to <12 months of age is supported by an open-label, multicenter study of LIVMARLI which showed a similar safety, tolerability and pharmacokinetic profile to patients with ALGS >12 months of age.

The safety and effectiveness of LIVMARLI have not been established in patients with ALGS less than 3 months of age.

PFIC

The safety and effectiveness of LIVMARLI for the treatment of cholestatic pruritus in PFIC have been established in pediatric patients aged 12 months of age and older. Use of LIVMARLI in this population is supported by evidence from Trial 2 in patients 1 to <18 years of age that included 26 weeks of placebo-controlled safety and efficacy data [see Adverse Reactions (6.1) and Clinical Studies (14.2)].

The 19 mg/mL formulation of LIVMARLI should be used in patients with PFIC in order to minimize exposure to excipients, including propylene glycol. Patients less than 5 years of age are at highest risk for propylene glycol toxicity. The total daily intake of propylene glycol from all sources should be considered for managing the risk of propylene glycol toxicity [see Warnings and Precautions (5.4)].

The safety and effectiveness of LIVMARLI have not been established in patients with PFIC younger than 12 months of age.

8.5 Geriatric Use

The safety and effectiveness of LIVMARLI for the treatment of pruritus in ALGS or PFIC in adult patients, 65 years of age and older, have not been established.

8.6 Hepatic impairment

Clinical studies of LIVMARLI included ALGS or PFIC patients with impaired hepatic function at baseline. The efficacy and safety in ALGS or PFIC patients with clinically significant portal hypertension and in patients with decompensated cirrhosis have not been established. LIVMARLI is contraindicated in patients with prior or active hepatic decompensation events [see Dosage and Administration (2.5), Contraindications (4), Warnings and Precautions (5.1), and Clinical Studies (14)].

10 OVERDOSAGE

Single doses of maralixibat up to 500 mg, approximately 18-fold higher than the recommended dose, have been administered in healthy adults and were tolerated without a meaningful increase in adverse effects when compared to lower doses. If an overdose occurs, discontinue LIVMARLI, monitor the patient for any signs and symptoms and institute general supportive measures if needed.

LIVMARLI contains propylene glycol as an excipient. In cases of suspected overdose, monitor for signs of propylene glycol toxicity, including hemolysis, hyperosmolarity with anion gap metabolic acidosis, acute kidney injury, and CNS toxicity. Discontinue LIVMARLI if propylene glycol toxicity is suspected.

11 DESCRIPTION

LIVMARLI (maralixibat) is an ileal bile acid transporter (IBAT) inhibitor. Maralixibat is present as a chloride salt with the chemical name 1-[[4-[[4-[(4R,5R)-3,3-dibutyl-7-(dimethylamino)-2,3,4,5-tetrahydro-4-hydroxy-1,1-dioxido-1-benzothiepin-5-yl]phenoxy]methyl]phenyl]methyl]-4-aza-1-azoniabicyclo[2.2.2]octane chloride. The molecular formula of maralixibat chloride is C40H56ClN3O4S with a molecular weight of 710.42. It has the following chemical structure:

LIVMARLI oral solution is supplied in a multiple-dose bottle containing 9.5 mg of maralixibat per mL (equivalent to 10 mg of maralixibat chloride per mL), or containing 19 mg of maralixibat per mL (equivalent to 20 mg of maralixibat chloride per mL). The oral solution contains the following inactive ingredients: edetate disodium, grape flavor, propylene glycol, purified water, and sucralose. The pH of the oral solution is 3.8 – 4.8.

LIVMARLI tablets are available in 10 mg, 15 mg, 20 mg and 30 mg strengths of maralixibat (equivalent to 10.5 mg, 15.8 mg, 21 mg, and 31.6 mg maralixibat chloride, respectively). The tablets contain the following inactive ingredients: crospovidone, glyceryl distearate, lactose monohydrate, microcrystalline cellulose, and silicon dioxide.

12 CLINICAL PHARMACOLOGY

12.1 Mechanism of Action

Maralixibat is a reversible inhibitor of the ileal bile acid transporter (IBAT). It decreases the reabsorption of bile acids (primarily the salt forms) from the terminal ileum.

Pruritus is a common symptom in patients with ALGS or PFIC and the pathophysiology of pruritus in patients with ALGS or PFIC is not completely understood. Although the complete mechanism by which maralixibat improves pruritus in ALGS or PFIC patients is unknown, it may involve inhibition of the IBAT, which results in decreased reuptake of bile salts, as observed by a decrease in serum bile acids [see Clinical Pharmacology (12.2)].

12.2 Pharmacodynamics

ALGS

In Trial 1, pediatric patients with ALGS were administered open-label treatment with LIVMARLI 380 mcg/kg once daily for 13 weeks after an initial 5-week dose-escalation period [see Clinical Studies (14.1)]. At baseline, serum bile acids were highly variable among patients ranging from 20 to 749 µmol/L and mean (SD) serum bile acid level was 283 (210.6) µmol/L. Serum bile acid levels decreased from baseline in the majority of patients as early as at Week 12 and the reduction in serum bile acids was generally maintained for the treatment period.

PFIC

In Trial 2, pediatric patients with PFIC were administered LIVMARLI 570 mcg/kg or placebo twice daily for up to 22 weeks after an initial 4–6-week dose escalation period [see Clinical Studies (14.2)]. At baseline, serum bile acids concentrations were highly variable among patients ranging from 4 to 504 µmol/L and mean (SD) serum bile acid level was 253 (136) µmol/L. Serum bile acid concentrations decreased from baseline in the majority of patients as early as at Week 2; while the concentrations fluctuated, the reduction in serum bile acids was generally maintained for the treatment period.

12.3 Pharmacokinetics

Because of the low systemic absorption of maralixibat, pharmacokinetic parameters cannot be reliably calculated at the recommended doses. Concentrations of maralixibat in the pediatric ALGS and PFIC patients were below the limit of quantification (0.25 ng/mL) in the majority of plasma samples.

Following single dose administration of maralixibat oral solution in healthy adults at doses ranging from 1 mg to 500 mg, plasma concentrations of maralixibat were below the limit of quantification (0.25 ng/mL) at doses less than 20 mg and PK parameters could not be reliably estimated.

Following single dose administration of 30 mg maralixibat oral solution under fasted condition, median Tmax was 0.75 hour and mean (SD) Cmax and AUClast were 1.65 (1.10) ng/mL and 3.43 (2.13) ng·h/mL, respectively.

Absorption

Maralixibat is minimally absorbed and plasma concentrations are often below the limit of quantification (0.25 ng/mL) after single or multiple doses at recommended doses.

Oral Solution: Following a single oral administration of maralixibat 30, 45, and 100 mg liquid formulation under fasted condition, AUClast and Cmax increased in a dose-dependent manner with increase of 4.6-and 2.4-fold, respectively, following a 3.3-fold dose increase from 30 to 100 mg.

No accumulation of maralixibat was observed following repeated oral administration of maralixibat in healthy adults at doses up to 100 mg once-daily.

Tablet: After a single 100 mg dose of maralixibat tablet under fasted condition, mean (SD) AUCinf and Cmax were 13.2 (8.2) ng·h/mL and 3.0 (2.2) ng/mL, respectively. Following a single dose of maralixibat oral solution (99.75 mg) under the same conditions, mean (SD) AUCinf and Cmax were 18.4 (13.2) ng·h/mL and 4.3 (2.7) ng/mL, respectively. Given the local site of action of maralixibat, the slightly lower exposure afforded by the tablet compared to the oral solution is not clinically meaningful.

Effect of Food

Concomitant administration of a high-fat meal with a single dose of maralixibat oral solution decreased both the rate and extent of absorption. AUC and Cmax of maralixibat values in the fed state were 64.8% to 85.8% lower relative to oral administration of 30 mg in fasted conditions. The effect of food on the changes of systemic exposures to maralixibat is not clinically significant [see Dosage and Administration (2.1, 2.3)].

Distribution

Maralixibat shows high binding (91%) to human plasma proteins in vitro.

Elimination

Following a single dose of 30 mg maralixibat oral solution in healthy adults, the mean half-life (t1/2) was 1.6 hours.

Metabolism

No maralixibat metabolites have been detected in plasma. Three minor metabolites, accounting for <3% of maralixibat-associated fecal radioactivity in total, were identified following administration of [^14C]maralixibat as an oral solution.

Excretion

Fecal excretion was found to be the major route of elimination. Following a single dose of 5 mg ^14C-maralixibat as an oral solution, 73% of the dose was excreted in the feces with 0.066% excreted in the urine. 94% of the fecal excretion was as unchanged maralixibat.

Specific Populations

Patients with Renal Impairment

The pharmacokinetics of maralixibat were not studied in patients with impaired renal function, including those with end-stage renal disease (ESRD) or those on hemodialysis.

Drug Interaction Studies

Effect of Other Drugs on Maralixibat

Maralixibat is not a substrate of the drug transporters MDR1 (P-gp), BCRP, OATP1B1, OATP1B3, or OATP2B2; therefore, concomitant drug products are not predicted to affect the disposition of maralixibat.

Effect of Maralixibat on Other Drugs

In vitro, maralixibat did not induce CYP isoforms 1A2, 2B6, or 3A4, nor inhibit CYP isoforms 1A2, 2B6, 2C8, 2C9, 2C19 or 2D6 at clinically relevant concentrations. Maralixibat inhibits CYP3A4 in vitro, however clinically relevant effects on the pharmacokinetics of CYP3A4 substrates are unlikely. In vitro, maralixibat did not inhibit the transporters MDR1 (P-gp), BCRP, OAT1, OAT3, OATP1B1, OATP1B3, PEPT1, OCT1, OCT2, OCT3, OCTN1, OCTN2, MRP2, MATE1, or MATE2-K at clinically relevant concentrations.

Maralixibat inhibits the drug transporter OATP2B1 in vitro, which can potentially result in reduced absorption of drugs that rely on OATP2B1-mediated uptake in the GI tract. In clinical studies coadministration of 4.75 mg maralixibat (once daily in the morning) with daily doses of either simvastatin, or lovastatin in the evening, did not have a clinically relevant effect on the pharmacokinetics of these statins and their metabolites. Coadministration of 4.75 mg maralixibat did not affect pharmacokinetics of atorvastatin. However, the effect of maralixibat on the pharmacokinetics of OATP2B1 substrates at higher doses has not been evaluated in a clinical study.

12.5 Pharmacogenomics

PFIC is a heterogenous disease caused by homozygous or compound heterozygous variants, with different PFIC subtypes occurring in the general population. PFIC1 is caused by variants in the aminophospholipid flippase (ATP8B1) gene, which encodes the Familial Intrahepatic Cholestasis 1 (FIC1) protein, while PFIC2 results from variants in the ABCB11 gene, which encodes the Bile Salt Export Pump (BSEP) protein. PFIC2 is further categorized into BSEP subgroups based on specific variants. The BSEP-1 subgroup includes patients with at least one p.D482G (c.1445A>G) or p.E297G (c.890A>G) variant, BSEP-2 includes patients with at least one missense variant other than p.D482G or p.E297G (non BSEP-1), and BSEP-3 includes patients with variants that are predicted to encode a non-functional protein. PFIC3 is caused by variants in the ABCB4 gene, which encodes multidrug resistance protein 3 (MDR3). PFIC4 is caused by variants in the tight junction protein 2 gene (TJP2), which encodes TJP2. PFIC6 is caused by variants in myosin 5B (MYO5B), which encodes MYO5B. Patients can be clinically diagnosed with PFIC without a known pathogenic variant.

PFIC2 is the most common subtype accounting for 37-90% of patients with PFIC. The prevalence of BSEP-1, BSEP-2, and BSEP-3 subgroups are approximately 27.3%, 51.5%, and 21.2%, respectively, based on data from a global consortium characterizing the natural history of severe BSEP deficiency.

13 NONCLINICAL TOXICOLOGY

13.1 Carcinogenesis, Mutagenesis, Impairment of Fertility

Carcinogenesis

Maralixibat chloride was not tumorigenic in a 2-year oral carcinogenicity study in rats with administration of up to 100 mg/kg/day (approximately 233 to 870 times the maximum recommended dose based on AUC). In a 26-week oral carcinogenicity study in TgRasH2 mice with doses of up to 25 (males) or 75 (females) mg/kg/day, no drug-related tumors were observed following administration of maralixibat chloride.

Mutagenesis

Maralixibat chloride was negative in in vitro (bacterial reverse mutation, chromosomal aberration in mammalian cells) and in vivo (rat bone marrow micronucleus) assays.

Impairment of Fertility

No effects on fertility were observed in female rats treated orally with up to 2000 mg/kg/day or in male rats treated orally with up to 750 mg/kg/day.

14 CLINICAL STUDIES

14.1 Alagille Syndrome

The efficacy of LIVMARLI was assessed in Trial 1 (NCT02160782), which consisted of an 18-week open-label treatment period; a 4-week randomized, double-blind, placebo-controlled drug-withdrawal period; a subsequent 26-week open-label treatment period; and a long-term open-label extension period.

Thirty-one pediatric ALGS patients with cholestasis and pruritus were enrolled, with 90.3% of patients receiving at least one medication to treat pruritus at study entry. All patients had JAGGED1 mutation. Patients were administered open-label treatment with LIVMARLI 380 mcg/kg once daily for 13 weeks after an initial 5-week dose-escalation period; two patients discontinued treatment during this first 18 weeks of open-label treatment. The 29 patients who completed the open-label treatment phase were then randomized to continue treatment with LIVMARLI or receive matching placebo during the 4-week drug withdrawal period at Weeks 19-22 (n=16 placebo, n=13 LIVMARLI). All 29 patients completed the randomized, blinded drug withdrawal period; subsequently, patients received open-label LIVMARLI at 380 mcg/kg once daily for an additional 26 weeks.

Randomized patients had a median age of 5 years (range: 1 to 15 years) and 66% were male. The baseline mean (standard deviation [SD]) of liver test parameters were as follows: serum bile acid levels 280 (213) µmol/L, AST 158 (68) U/L, ALT 179 (112) U/L, Gamma Glutamyl Transferase (GGT) 498 (399) U/L, and TB 5.6 (5.4) mg/dL.

Given the patients’ young age, a single-item observer-reported outcome was used to measure patients’ pruritus symptoms as observed by their caregiver twice daily (once in the morning and once in the evening) on the Itch Reported Outcome Instrument (ItchRO[Obs]). Pruritus symptoms were assessed on a 5-point ordinal response scale, with scores ranging from 0 (none observed or reported) to 4 (very severe). Patients were included in Trial 1 if their average pruritus score was greater than 2.0 (moderate) in the 2 weeks prior to baseline.

The average of the worst daily ItchRO(Obs) pruritus scores was computed for each week. For randomized patients, the mean (SD) at baseline (pre-treatment) was 3.1 (0.5) and the mean (SD) at Week 18 (pre-randomized withdrawal period) was 1.4 (0.9). On average, patients administered LIVMARLI for 22 weeks maintained pruritus reduction whereas those in the placebo group who were withdrawn from LIVMARLI after Week 18 returned to baseline pruritus scores by Week 22. Results from the placebo-controlled period are presented in Table 7. After re-entering the open-label treatment phase, both randomized treatment groups had similar mean pruritus scores by Week 28, the first week placebo patients received the full dosage of LIVMARLI after withdrawal. These observer-rated pruritus results are supported by similar results on patient-rated pruritus in patients 5 years of age and older who were able to self-report their itching severity.

Table 7: Weekly Average of Worst Daily ItchRO(Obs) Pruritus Severity Scores in Trial 1
 | Maralixibat; (N=13) | Placebo; (N=16) | Mean Difference
Week 22, Mean (95% CI) | 1.6 (1.1, 2.1) | 3.0 (2.6, 3.5)
Change from Week 18 to Week 22, Mean (95% CI) | 0.2 (-0.3, 0.7) | 1.6 (1.2, 2.1) | -1.4 (-2.1, -0.8)
Results based on an analysis of covariance model with treatment group and Week 18 average worst daily pruritus score as covariates

14.2 Progressive Familial Intrahepatic Cholestasis

The efficacy of LIVMARLI was assessed in Trial 2 (NCT03905330), a 26-week randomized, placebo-controlled trial.

Efficacy was evaluated in 64 patients with documented molecular diagnosis of PFIC with presence of biallelic known pathogenic variants; this included 31 non-truncated PFIC2 patients (i.e., excluding patients with BSEP3) and 33 patients with PFIC1 (n=13), PFIC3 (n=9), PFIC4 (n=7), or PFIC6 (n=4) [see Clinical Pharmacology (12.5)]. Additional patients with BSEP3 (n=9), prior surgical diversion (n=8), heterozygous subjects (n=2), or no variants associated with cholestasis (n=8) were included for evaluation in a supplemental cohort [see Adverse Reactions (6.1)].

Patients were randomized to receive maralixibat orally 570 mcg/kg (n=33) or placebo (n=31) twice daily. 53% of pediatric patients were females. Most patients were on stable ursodeoxycholic acid (89.1%) or rifampicin (51.6%) therapy at baseline. The baseline mean (standard deviation [SD]) of liver test parameters were as follows: serum bile acid levels 263 (143) μmol/L, AST 113 (82) U/L, ALT 107 (87) U/L, and TB 4.1 (4.1) mg/dL, DB 3.0 (3.1) mg/dL.

Given the patients’ young age, a single-item observer-reported outcome was used to measure patients’ pruritus symptoms as observed by their caregiver twice daily (once in the morning and once in the evening) on the Itch Reported Outcome Instrument (ItchRO[Obs]). Pruritus symptoms were assessed on a 5-point ordinal response scale, with scores ranging from 0 (none observed or reported) to 4 (very severe). Patients were included in Trial 2 if their average pruritus score was greater than or equal to 1.5 in the 4 weeks prior to baseline.

Table 8 presents the results of the comparison between LIVMARLI and placebo on the mean change in the average morning ItchRO(Obs) severity score between baseline and Weeks 15–26. For the outcome summarized over Weeks 15-26, the average morning ItchRO(Obs) severity score for each patient was calculated by: (Step 1) averaging the morning scores within a week; (Step 2) averaging 4 weekly morning scores to yield a single 4-week score; and finally (Step 3) averaging the three 4-week average morning scores (Weeks 15-18, Weeks 19-22, Weeks 23-26). The baseline average itching scores for each patient was calculated by averaging the morning ItchRO(Obs) score obtained in Step 2 across the 4 weeks prior to the first dose of the study. Patients treated with LIVMARLI demonstrated greater improvement in pruritus compared with placebo.

Table 8: Average Morning ItchRO(Obs) Pruritus Severity Scores in Trial 2
 | Maralixibat; (N=33) | Placebo; (N=31)
Baseline Mean | 2.9 | 2.7
Change from baseline to Weeks 15-26a
Mean (95% CI) | -1.8 (-2.2, -1.4) | -0.6 (-1.0, -0.2)
Mean difference from Placebo (95% CI) | -1.2 (-1.7, -0.7)
p-value | <0.0001
aResults based on least squares means from an analysis of a mixed-effect model for repeated measures (MMRM). Model adjusts for treatment group, visit, treatment group-by-visit interaction, baseline 4-week average morning ItchRO(Obs) severity score, baseline score-by-visit interaction, and PFIC type.

Figure 1 displays the means (95% confidence intervals) of patients’ average morning ItchRO(Obs) severity scores in each treatment group for each 4-6 week time period.

Figure 1. Mean of the Average Morning ItchRO(Obs) Pruritus Severity Scores Over Time in PFIC 1, 2, 3, 4, and 6

Note: Figure 1 presents least squares mean (95% CI) estimates from a mixed model for repeated measures (MMRM) with observed value as the dependent variable and fixed categorical effects of treatment group, time period, treatment-by-time period interaction, and PFIC type.

Although the number of patients with BSEP3 in Trial 2 were limited, improvement in pruritus was not observed in 5 patients with BSEP3 who received LIVMARLI compared to 4 patients with BSEP3 who received placebo for 26 weeks.

16 HOW SUPPLIED/STORAGE AND HANDLING

LIVMARLI Oral Solution

LIVMARLI is a clear, colorless to yellow oral solution.

For ALGS: 9.5 mg per mL

- Each amber plastic bottle contains LIVMARLI oral solution at a concentration of 9.5 mg per mL.
- One 30 mL amber plastic bottle: NDC 79378-110-01

For PFIC: 19 mg per mL

- Each amber plastic bottle contains LIVMARLI oral solution at a concentration of 19 mg per mL.
- One 30 mL amber plastic bottle: NDC 79378-111-01

LIVMARLI Tablets

- 10 mg are white to off-white round tablets debossed with MRX on one side, 10 on the other side.
Bottles of 30 tablets: NDC 79378-210-30
- 15 mg are white to off-white modified oval tablets debossed with MRX on one side, 15 on the other side.
Bottles of 30 tablets: NDC 79378-215-30
- 20 mg are white to off-white round tablets debossed with MRX on one side, 20 on the other side.
Bottles of 30 tablets: NDC 79378-220-30
- 30 mg are white to off-white round tablets debossed with MRX on one side, 30 on the other side.
Bottles of 30 tablets: NDC 79378-230-30

Storage and Handling

Store unopened LIVMARLI oral solution and tablets between 20°C and 25°C (68°F and 77°F), excursion permitted between 15°C and 30°C (59°F and 86°F) [see USP Controlled Room Temperature].

Discard any remaining LIVMARLI oral solution 100 days after opening the bottle [see Dosage and Administration (2.5)].

17 PATIENT COUNSELING INFORMATION

Advise the patient or their caregiver(s) to read the FDA-approved patient labeling (Patient Information and Instructions for Use).

Administration Instructions

Advise patients or their caregivers(s) to:

- Take LIVMARLI 30 minutes prior to a meal once or twice daily as prescribed.
- For LIVMARLI oral solution, use a calibrated measuring device (0.5 mL, 1 mL or 3 mL oral dispenser) provided by the pharmacist to measure and deliver the prescribed dose accurately [see Dosage and Administration (2.2, 2.3, 2.5)].
- Take LIVMARLI at least 4 hours before or 4 hours after taking a bile acid binding resin (e.g., cholestyramine, colesevelam, or colestipol) [see Drug Interactions (7.1)].
- Store the opened LIVMARLI oral solution bottle below 30⁰C (86⁰F). Discard any unused LIVMARLI 100 days after opening the oral solution bottle [see How Supplied/Storage and Handling (16)].

Hepatotoxicity

Advise patients or their caregiver(s) that liver tests should be obtained before starting LIVMARLI and periodically during LIVMARLI therapy. Inform patients or their caregiver(s) of the risk of hepatotoxicity that could be fatal and that they will need to undergo monitoring for liver injury. Instruct patients or their caregiver(s) to immediately report any signs or symptoms of severe liver injury to their healthcare provider [see Warnings and Precautions (5.1)].

Gastrointestinal Adverse Reactions

Advise patients or their caregiver(s) to notify their healthcare provider if they experience a new onset or worsening of gastrointestinal symptoms (abdominal pain, vomiting, bloody stool, and diarrhea) [see Warnings and Precautions (5.2)].

Fat Soluble Vitamin (FSV) Deficiency

Advise patients or their caregiver(s) that INR (for vitamin K) and serum levels of vitamins A, D, E will be obtained before starting treatment and periodically during treatment to assess for FSV deficiency [see Warnings and Precautions (5.3)]. Inform patients or their caregiver(s) that they may bleed more easily, may bleed longer, or have a bone fracture. Advise patients or their caregiver(s) to call their healthcare provider for any signs or symptoms of bleeding or report any fractures.

Rx only

Manufactured for:
Mirum Pharmaceuticals, Inc.
989 E. Hillsdale Blvd., Suite 300
Foster City, CA 94404

© 2025 Mirum Pharmaceuticals, Inc.
LIVMARLI® is a registered trademark of Mirum Pharmaceuticals, Inc.

LB00203 / LB00212

PATIENT INFORMATION
LIVMARLI® (liv-MAR-lee)
(maralixibat)
oral solution and tablets, for oral use

What is LIVMARLI?

- LIVMARLI is a prescription medicine used to treat:
  - cholestatic pruritus (itch) in patients 3 months of age and older with Alagille syndrome (ALGS).
  - cholestatic pruritus (itch) in patients 12 months of age and older with progressive familial intrahepatic cholestasis (PFIC).
- LIVMARLI is not for use in PFIC type 2 patients who have a severe defect in the bile salt export pump (BSEP) protein.
- It is not known if LIVMARLI is safe and effective in children with ALGS who are under 3 months of age.
- It is not known if LIVMARLI is safe and effective in children with PFIC who are under 12 months of age.
- It is not known if LIVMARLI is safe and effective in adults 65 years of age and older.

Before taking LIVMARLI, tell your healthcare provider about all of your medical conditions, including if you:

- are pregnant or plan to become pregnant. It is not known if LIVMARLI will harm your unborn baby. Tell your healthcare provider right away if you think that you are pregnant.
- are breastfeeding or plan to breastfeed. It is not known if LIVMARLI passes into your breast milk. Talk with your healthcare provider about the best way to feed your baby if you take LIVMARLI.

Tell your healthcare provider about all medicines that you take, including prescription and over-the-counter medicines, vitamins, and herbal supplements. Know the medicines you take. Keep a list of them to show your healthcare provider and pharmacist when you get a new medicine. LIVMARLI may affect the way some other medicines work, and some other medicines may affect the way LIVMARLI works.

How should you take LIVMARLI?

- LIVMARLI is available in oral solution and tablet.

Read the Instructions for Use that comes with LIVMARLI for information about the right way to prepare and take LIVMARLI oral solution.

- LIVMARLI oral solution comes in 2 different strengths:
  - LIVMARLI oral solution 9.5 mg/mL for use in ALGS
  - LIVMARLI oral solution 19 mg/mL for use in PFIC
- Before you take LIVMARLI oral solution for the first time, talk to your healthcare provider or pharmacist about how to measure the prescribed dose.
- Take LIVMARLI exactly as your healthcare provider tells you to.
- Your healthcare provider may start you on a low dose of LIVMARLI and then increase the dose, especially if you have not taken LIVMARLI.
- Do not change your dose of LIVMARLI unless your healthcare provider tells you to.
- LIVMARLI is taken by mouth, 1 or 2 times each day (if 2 times per day, take in the morning and evening), 30 minutes before a meal.
- If you miss a dose of LIVMARLI and you take LIVMARLI 1-time a day:
  - If it is 12 hours or less from the time you usually take LIVMARLI, take the missed dose as soon as possible. Then take your next dose at the usual time.
  - If it is more than 12 hours from the time you usually take LIVMARLI, do not take the missed dose. Take your next dose at the usual time.
- If you miss a dose of LIVMARLI and you take LIVMARLI 2-times a day:
  - If it is 6 hours or less from the time you usually take LIVMARLI, take the missed dose as soon as possible. Then take your next dose at the usual time.
  - If it is more than 6 hours from the time you usually take LIVMARLI, do not take the missed dose. Take your next dose at the usual time.
- If you take a medicine that lowers cholesterol by binding bile acids, such as cholestyramine, colesevelam, or colestipol, take it at least 4 hours before or 4 hours after you take LIVMARLI. Ask your healthcare provider if you are not sure if you take these medicines.
- If you take too much LIVMARLI, call your healthcare provider or go to the nearest emergency room right away.
- After opening the LIVMARLI oral solution bottle, store below 30°C (86°F). Throw away any remaining LIVMARLI oral solution 100 days after first opening the bottle.

What are the possible side effects of LIVMARLI?
LIVMARLI can cause serious side effects, including:

- Liver injury. Changes in certain liver tests are common in patients with ALGS and in patients with PFIC but may worsen during treatment with LIVMARLI. These changes may be a sign of liver injury and can be serious or may lead to liver transplant or death. Your healthcare provider should do blood tests and physical exams before starting and during treatment with LIVMARLI to check your liver function. Tell your healthcare provider right away if you get any signs or symptoms of liver problems, including:
  - nausea or vomiting
  - your skin or the white part of your eye turns yellow
  - dark or brown urine
  - pain on the right side of your stomach (abdomen)
  - fullness, bloating, or fluid in your stomach area (ascites)
  - loss of appetite
  - bleeding or bruising more easily than normal, including vomiting blood
- Stomach and intestinal (gastrointestinal) problems. LIVMARLI can cause stomach and intestinal problems, including diarrhea and stomach pain during treatment. Diarrhea can also cause the loss of too much body fluid (severe dehydration). Your healthcare provider should check your stool for blood and monitor you for too much body fluid loss.
  Tell your healthcare provider right away if you have any new or worsening signs or symptoms of stomach and intestinal problems including:

- diarrhea

- more frequent bowel movements than usual

- stools that are black, tarry, sticky, or have blood or mucous

- severe stomach-area pain or tenderness

Tell your healthcare provider if you have any signs and symptoms of a loss of too much body fluid including:

- vomiting
- diarrhea

- urinating less often than usual
- headache

- dizziness

- A condition called Fat Soluble Vitamin (FSV) Deficiency caused by low levels of certain vitamins (vitamin A, D, E, and K) stored in body fat. FSV deficiency is common in patients with ALGS and in patients with PFIC but may worsen during treatment with LIVMARLI. Your healthcare provider should do blood tests before starting and during treatment with LIVMARLI.
  Other common side effects of FSV deficiency reported during treatment with LIVMARLI were bone fractures and bleeding. Tell your healthcare provider if you have signs or symptoms of bleeding or any fractures.

Your healthcare provider may change your dose, or temporarily or permanently stop treatment with LIVMARLI if you have certain side effects.
These are not all of the possible side effects of LIVMARLI. For more information, ask your healthcare provider or pharmacist. Call your doctor for medical advice about side effects. You may report side effects to FDA at 1-800-FDA-1088.

How should I store LIVMARLI?

- Store unopened LIVMARLI oral solution and tablet bottles at room temperature between 68ºF and 77ºF (20ºC and 25°C).
- After opening the LIVMARLI oral solution bottle, store below 30ºC (86ºF). Throw away any remaining LIVMARLI oral solution 100 days after first opening the bottle.

Keep LIVMARLI and all medicines out of the reach of children.

General information about the safe and effective use of LIVMARLI.
Medicines are sometimes prescribed for purposes other than those listed in a Patient Information leaflet. Do not use LIVMARLI for a condition for which it was not prescribed. Do not give LIVMARLI to other people, even if they have the same symptoms that you have. It may harm them. You can ask your healthcare provider or pharmacist for information about LIVMARLI that is written for health professionals.

What are the ingredients in LIVMARLI?
Active ingredients: maralixibat chloride.
Oral Solution inactive ingredients: edetate disodium, grape flavor, propylene glycol, purified water, and sucralose.

Tablet inactive ingredients crospovidone, glyceryl distearate, lactose monohydrate, microcrystalline cellulose, and silicon dioxide.

Manufactured for: Mirum Pharmaceuticals, Inc., 989 E. Hillsdale Blvd., Suite 300, Foster City, CA 94404

For more information, go to www.LIVMARLI.com or call 1-855-MRM-4YOU

LB00203 / LB00212

This Patient Information has been approved by the U.S. Food and Drug Administration

Revised: April 2025

INSTRUCTIONS FOR USE
LIVMARLI® [liv-MAR-lee]
(maralixibat)
oral solution

This Instructions for Use contains information on how to take LIVMARLI. Read this Instructions for Use before you start taking LIVMARLI for the first time and each time you get a refill. There may be new information. This information does not take the place of talking to your healthcare provider about your medical condition or treatment.
LIVMARLI is available in two strengths:

- LIVMARLI 9.5 mg/mL is for the treatment of Alagille Syndrome.
- LIVMARLI 19 mg/mL is for the treatment of Progressive Familial Intrahepatic Cholestasis.

Follow your healthcare provider's instructions for the dose of LIVMARLI to give.

Ask your healthcare provider or pharmacist if you have questions about how to prepare or give the prescribed dose of LIVMARLI.

Important information about measuring LIVMARLI

- Before you give LIVMARLI for the first time, talk to your healthcare provider or pharmacist about how to correctly measure your prescribed dose.
- You may be given 1 or more dosing dispensers of different sizes as shown in Table 1 below. Always use the correct dosing dispenser size provided with LIVMARLI based on your current prescribed dose.

Table 1

Dose (mL)

Dosing dispenser size (mL)

0.1 to 0.5

0.5

0.6 to 1

1

1.25 to 3

3

- Your prescribed dose may change over time. Use the table above to choose the correct dosing dispenser size for your prescribed dose.
- If you do not have the correct dosing dispenser size for your prescribed dose, contact your healthcare provider or pharmacist.
- The dosing dispenser may be used for 100 days if cleaned correctly (see Section C). After 100 days, replace the dosing dispenser with a new one. A new replacement dosing dispenser may be used within the 100 days if necessary.
- Do not use a household teaspoon or any other dosing device to measure the dose.
- Do not open more than 1 bottle of LIVMARLI at a time.
- Do not give more than the prescribed dose.
- Do not use LIVMARLI after 100 days of first opening the bottle or after the throw away (discard) date listed on the pharmacy label (see Section D).
- When you start a new bottle of LIVMARLI, use a new dosing dispenser.

Storage information

- Store unopened LIVMARLI at room temperature, between 68°F and 77°F (20°C and 25°C).
- After opening the LIVMARLI bottle, store below 86°F (30°C) and throw away (discard) any remaining LIVMARLI after 100 days.
- Store the dosing dispenser in a clean, dry place when not in use.

Keep LIVMARLI and all medicines out of the reach of children.

You will receive

LIVMARLI oral solution

Each package of LIVMARLI contains:

LIVMARLI (9.5 mg/mL or 19 mg/mL):

Dosing dispensers, provided separately by your pharmacist:

Note: Dosing dispenser sizes shown are for example only.

Section A: Prepare the bottle

1. Remove the LIVMARLI bottle from the box (See Figure A).

Note: The LIVMARLI bottle may not be in a box.

Figure A

2. Write the date (bottle open date) on the LIVMARLI bottle (See Figure B).

Note: The date of first opening or a throw away (discard) date may already be written on the bottle label by your pharmacist.

Figure B

3. Remove the plastic seal from the bottle (See Figure C).

Note: Your pharmacist may have already removed the plastic seal from the bottle.

Figure C

Section B: Prepare and give LIVMARLI

Step 1: Draw the dose

1.1:

Open the bottle by pushing down firmly on the child-resistant cap and turning the cap to the left (counter-clockwise) (See Figure D).
Do not throw away the child-resistant cap.

Figure D

1.2:

If using a new dosing dispenser, remove the dosing dispenser from the wrapper (See Figure E). Throw away (dispose of) the wrapper in household trash.

Figure E

If using a used dosing dispenser, make sure the dosing dispenser has been cleaned (See Section C).
If there is a cap on the dosing dispenser, remove it and throw away (dispose of) the cap into the household trash (See Figure F).
Important:

- Make sure you use the correct dosing dispenser size for your prescribed dose (See Table 1).
- After 100 days, replace with a new dosing dispenser provided. A new replacement dosing dispenser may be used within the 100 days if necessary.
- Check the dosing dispenser for any damage to the barrel, plunger or tip (See Figure G). If you cannot see the dosage marking or if it becomes hard to move the plunger, replace with a new dosing dispenser.

Note: You can mark the prescribed dose on the dosing dispenser with a thin permanent marker to draw up the prescribed dose more easily.

Figure F

Figure G

1.3: Push the plunger down fully to remove air from the dosing dispenser (See Figure H).

Figure H

1.4:

Make sure the cap is removed from bottle and insert the tip of the dosing dispenser into the bottle. The tip of the dosing dispenser should fit securely into the hole of the bottle (See Figure I).

Figure I

1.5:

Keep the dosing dispenser in place and turn the bottle upside down (See Figure J).

Figure J

1.6:

Pull back the plunger slowly until the top of the plunger is even with the marking on the barrel of the dosing dispenser for your prescribed dose of LIVMARLI (See Figure K).
See Figure L on how to align the plunger with your prescribed dose.
Note: The medicine should appear colorless to light yellow and clear. If it is not, do not use the medicine and contact your pharmacist.

Figure K

Figure L

Note: Your dose may be different than the dose shown in the figures.

1.7:

Check the dosing dispenser for air bubbles. If you see any air bubbles, fully push the plunger so that the medicine flows back into the bottle and withdraw the prescribed dose (See Figure M).

Figure M

1.8:

When you have measured the correct dose, leave the dosing dispenser in the bottle, and turn the bottle right side up (See Figure N).

Figure N

1.9:

Carefully remove the dosing dispenser from the bottle by pulling straight up on the barrel of the dosing dispenser (See Figure O).
Do not push the dosing dispenser plunger during this step.

Figure O

Step 2: Give the dose

Note: LIVMARLI should be taken while sitting up or standing. After taking LIVMARLI wait a few minutes before lying down.

2.1:

Place the tip of the dosing dispenser against the inside of the cheek (See Figure P) and slowly push the plunger all the way in to give the entire dose of LIVMARLI (See Figure Q).

Figure P

Figure Q

2.2:

Swallow the dose.
If you are not sure the entire dose was swallowed, do not give another dose. Wait until the next scheduled dose.

2.3:

Place the child-resistant cap back on the bottle and turn the cap to the right (clockwise) (See Figure R).

Figure R

Section C: Cleaning instructions for the dosing dispenser

Step 1: Rinse dosing dispenser

1.1:

Fill a cup with water (See Figure S).

Figure S

1.2:

Clean the dosing dispenser by pulling back on the plunger slowly to fill the dosing dispenser with water from the cup (See Figure T).

Figure T

1.3:

Over a sink, push the water out of the dosing dispenser (See Figure U). Repeat several times to make sure that all of the LIVMARLI has been removed.

Figure U

Step 2: Dry the dosing dispenser

2.1:

Remove the plunger from the barrel of the dosing dispenser by pulling the plunger and barrel away from each other (See Figure V).

Figure V

2.2:

Shake off excess water (See Figure W).

Figure W

2.3:

Place the plunger and barrel on a clean, dry paper towel to air dry. Store the dosing dispenser in a clean, dry place until your next dose (See Figure X).

Figure X

Before you give the next dose, put the dosing dispenser back together by pushing the plunger into the barrel (See Figure Y).

Figure Y

Section D: Disposal

- Throw away (dispose of) the bottle of LIVMARLI following the steps below 100 days after first opened or after the throw away (discard) date listed on the pharmacy label, even if there is still medicine in it.
  1. Mix medicine with a substance such as dirt, cat litter, or used coffee grounds.
  2. Place the mixture in a container such as a sealed plastic bag.
  3. Delete all personal information on the prescription label of the empty medicine bottle, then throw away (dispose of) in the household trash or recycle the empty bottle.
- Throw away (dispose of) used dosing dispensers in the household trash.

This Instructions for Use has been approved by the U.S. Food and Drug Administration.

Revised: July 2024

LB00203 / LB00212

PRINCIPAL DISPLAY PANEL - 9.5 mg/mL Bottle Label

NDC 79378-110-01
Rx only

Livmarli®
(maralixibat) oral solution

9.5 mg/mL

Recommended Dosage:
See prescribing information

30 mL

PRINCIPAL DISPLAY PANEL - 19 mg/mL Bottle Label

NDC 79378-111-01
Rx only

Livmarli®
(maralixibat) oral solution

19 mg/mL

For use in Progressive Familial
Intrahepatic Cholestasis

30 mL

PRINCIPAL DISPLAY PANEL – 10 mg Bottle Label

GTIN: (01) 00379378210305; NDC 79378-210-30; Rx only
Livmarli (maralixibat) tablets; 10 mg; Recommended Dosage: See prescribing information; 30 tablets;
Each tablet contains 10 mg of maralixibat (equivalent to 10.5 mg of maralixibat chloride).
Store between 20°C and 25°C (68°F and 77°F); excursions permitted between 15°C and 30°C (59°F and 86°F) [see USP Controlled Room Temperature].
Inactive ingredients: crospovidone, glyceryl distearate, lactose monohydrate, microcrystalline cellulose, and silicon dioxide.
KEEP OUT OF REACH OF CHILDREN.
Manufactured for
Mirum Pharmaceuticals, Inc.
Foster City, CA 94404 Made in Canada

PRINCIPAL DISPLAY PANEL – 15 mg Bottle Label

GTIN: (01) 00379378215300; NDC 79378-215-30; Rx only
Livmarli (maralixibat) tablets; 15 mg; Recommended Dosage: See prescribing information; 30 tablets;
Each tablet contains 15 mg of maralixibat (equivalent to 15.8 mg of maralixibat chloride).
Store between 20°C and 25°C (68°F and 77°F); excursions permitted between 15°C and 30°C (59°F and 86°F) [see USP Controlled Room Temperature].
Inactive ingredients: crospovidone, glyceryl distearate, lactose monohydrate, microcrystalline cellulose, and silicon dioxide.
KEEP OUT OF REACH OF CHILDREN.
Manufactured for
Mirum Pharmaceuticals, Inc.
Foster City, CA 94404 Made in Canada

PRINCIPAL DISPLAY PANEL – 20 mg Bottle Label

GTIN: (01) 00379378220304; NDC 79378-220-30; Rx only
Livmarli (maralixibat) tablets; 20 mg; Recommended Dosage: See prescribing information; 30 tablets;
Each tablet contains 20 mg of maralixibat (equivalent to 21 mg of maralixibat chloride).
Store between 20°C and 25°C (68°F and 77°F); excursions permitted between 15°C and 30°C (59°F and 86°F) [see USP Controlled Room Temperature].
Inactive ingredients: crospovidone, glyceryl distearate, lactose monohydrate, microcrystalline cellulose, and silicon dioxide.
KEEP OUT OF REACH OF CHILDREN.
Manufactured for
Mirum Pharmaceuticals, Inc.
Foster City, CA 94404 Made in Canada

PRINCIPAL DISPLAY PANEL – 30 mg Bottle Label

GTIN: (01) 00379378230303; NDC 79378-230-30; Rx only
Livmarli (maralixibat) tablets; 30 mg; Recommended Dosage: See prescribing information; 30 tablets;
Each tablet contains 30 mg of maralixibat (equivalent to 31.6 mg of maralixibat chloride).
Store between 20°C and 25°C (68°F and 77°F); excursions permitted between 15°C and 30°C (59°F and 86°F) [see USP Controlled Room Temperature].
Inactive ingredients: crospovidone, glyceryl distearate, lactose monohydrate, microcrystalline cellulose, and silicon dioxide.
KEEP OUT OF REACH OF CHILDREN.
Manufactured for
Mirum Pharmaceuticals, Inc.
Foster City, CA 94404 Made in Canada